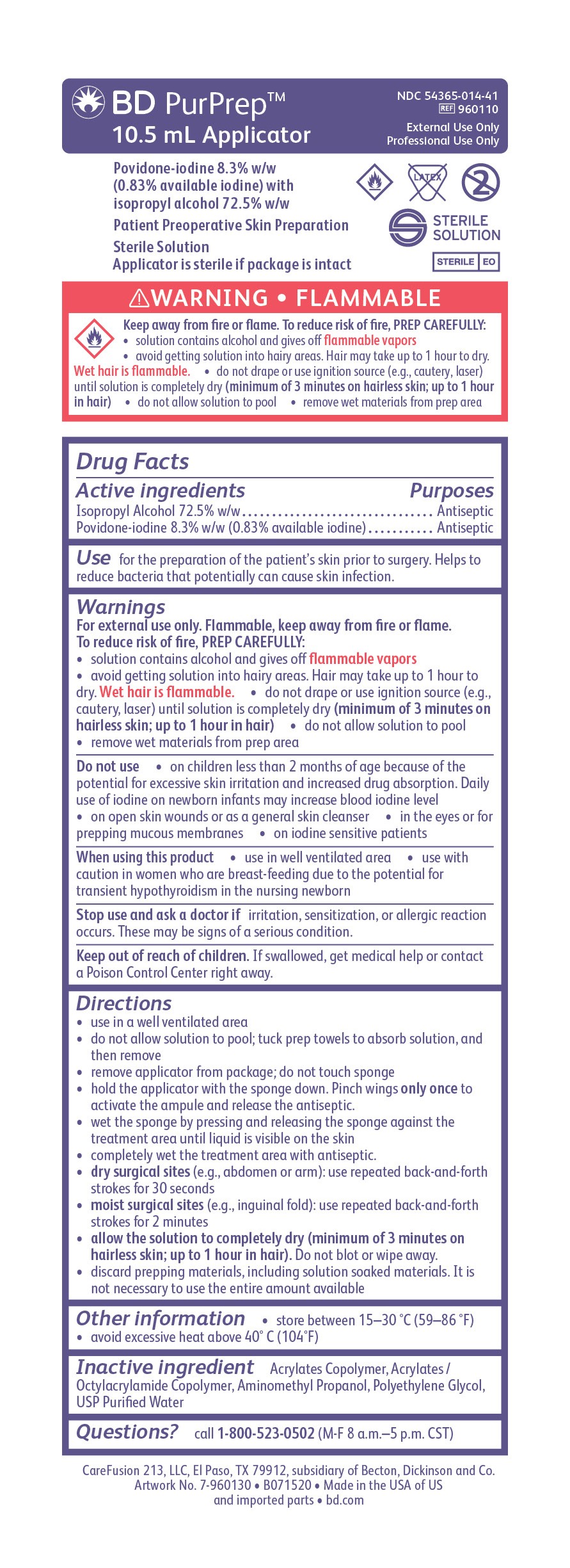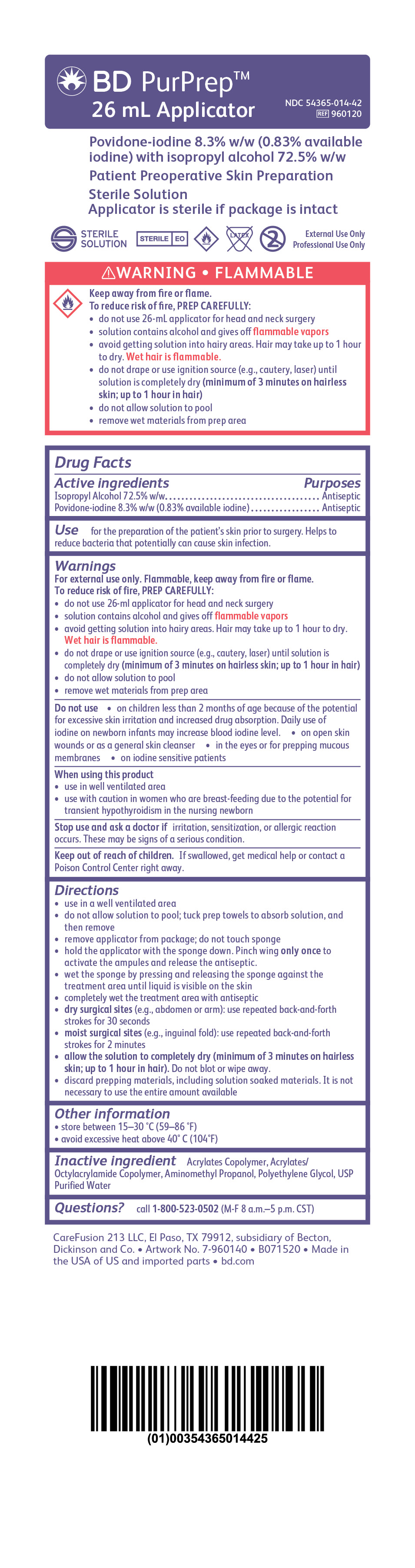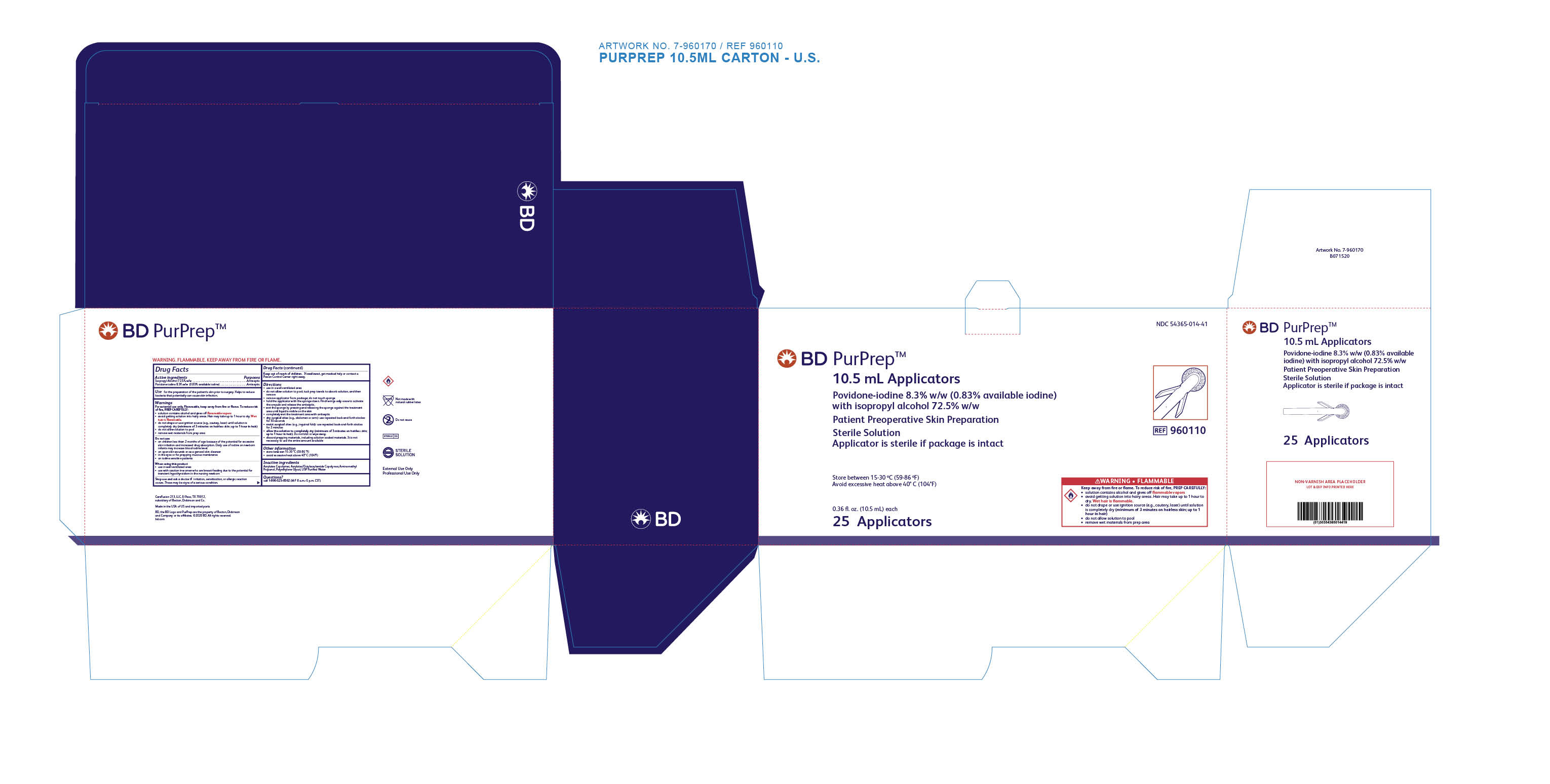 DRUG LABEL: PurPrep
NDC: 54365-014 | Form: SPONGE
Manufacturer: CareFusion 213 LLC
Category: otc | Type: HUMAN OTC DRUG LABEL
Date: 20251008

ACTIVE INGREDIENTS: ISOPROPYL ALCOHOL 725 mg/1 mL; POVIDONE-IODINE 8.3 mg/1 mL
INACTIVE INGREDIENTS: CARBOMER COPOLYMER TYPE A (ALLYL PENTAERYTHRITOL CROSSLINKED); POLYETHYLENE GLYCOL, UNSPECIFIED; WATER; AMINOMETHYLPROPANOL

BD PurPrep™ 10.5 mL Applicator
BD PurPrep™ 26 mL Applicator

Drug Facts

BD PurPrep™ 10.5 mL Applicator Active Ingredients

Isopropyl Alcohol 7.2% w/w

Povidone-Iodine 8.3% w/w (0.83% available iodine)

Purposes

Antiseptic

Antiseptic

Use

for the preparation of the patient's skin prior to surgery. Helps to reduce bacteria that potentially can cause skin infection.

Warnings

For external use only. Flammable, keep away from fire or flame.

To reduce risk of fire, PREP CAREFULLY:

- solution contains alcohol and gives off flammable vapors
- avoid getting solution into hairy areas. Hair may take up to 1 hour to dry. Wet hair is flammable.
- do not drape or use ignition source (e.g., cautery, laser) until solution is completely dry (minimum of 3 minutes on hairless skin; up to 1 hour in hair)
- do not allow the solution to pool
- remove wet materials from prep area

Do not use

- on children less than 2 months of age because of the potential for excessive skin irritation and increased drug absorption. Daily use of iodine on newborn infants may increase blood iodine level.
- on open skin wounds or as a general skin cleanser
- in the eyes or for prepping mucous membranes
- on iodine sensitive patients

When using this product

- use in well ventilated area
- use with caution in women who are breast-feeding due to the potential for transient hypothyroidism in the nursing newborn

Stop use and ask a doctor if

irritation, sensitization, or allergic reaction occurs. These may be signs of a serious condition.

Keep out of reach of children.

If swallowed, get medical help or contact a Poison Control Center right away.

Directions

- use in a well ventilated area
- do not allow solution to pool; tuck prep towels to absorb solution, and then remove
- remove applicator from package; do not touch sponge
- hold the applicator with the sponge down. Pinch wings only once to activate the ampule and release the antiseptic.
- wet the sponge by pressing and releasing the sponge against the treatment area until liquid is visible on the skin
- completely wet the treatment area with antiseptic
- dry surgical sites (e.g., abdomen or arm): use repeated back-and-forth strokes for 30 seconds
- moist surgical sites (e.g., inguinal fold): use repeated back-and-forth strokes for 2 minutes
- allow the solution to completely dry (minimum of 3 minutes on hairless skin; up to 1 hour in hair). Do not blot or wipe away.
- discard prepping materials, including solution soaked materials. It is not necessary to use the entire amount available.

Other information

- store between 15-30 °C (59-86 °F)
- avoid excessive heat above 40 °C (104 °F)

Inactive ingredients

Acrylates Copolymer, Acrylates/Octylacrylamide Copolymer, Aminomethyl Propanol, Polyethylene Glycol, USP Purified Water

Questions?

call 1-800-523-0502 (M-F 8 a.m.-5 p.m. CST)

BD PurPrep™ 26 mL Applicator Active Ingredients

Isopropyl Alcohol 72.5% w/w

Povidone-iodine 8.3% w/w (0.83% available iodine)

Purposes

Antiseptic

Antiseptic

Use

for the preparation of the patient's skin prior to surgery. Helps to reduce bacteria that potentially can cause skin infection.

Warnings

For external use only. Flammable, keep away from fire or flame.

T o reduce risk of fire, PREP CAREFULLY:

- do not use 26-mL applicator for head and neck surgery
- solution contains alcohol and gives off flammable vapors.
- avoid getting solution into hairy areas. Hair may take up to 1 hour to dry. Wet hair is flammable.
- do not drape or use ignition source (e.g., cautery, laser) until solution is completely dry (minimum of 3 minutes on hairless skin; up to 1 hour in hair)
- do not allow the solution to pool
- remove wet materials from prep area

Do not use

- on children less than 2 months of age because of the potential for excessive skin irritation and increased drug absorption. Daily use of iodine on newborn infants may increase blood iodine level.
- on open skin wounds or as a general skin cleanser
- in the eyes or for prepping mucous membranes
- on iodine sensitive patients

When using this product

- use in well ventilated area
- use with caution in women who are breast-feeding due to the potential for transient hypothyroidism in the nursing newborn

Stop use and ask a doctor if

irritation, sensitization, or allergic reaction occurs. These may be signs of a serious condition.

Keep out of reach of children.

If swallowed, get medical help or contact a Poison Control Center right away.

Directions

- use in a well ventilated area
- do not allow solution to pool; tuck prep towels to absorb solution, and then remove
- remove applicator from package; do not touch sponge
- hold the applicator with the sponge down. Pinch wings only once to activate the ampules and release the antiseptic.
- wet the sponge by pressing and releasing the sponge against the treatment area until liquid is visible on the skin
- completely wet the treatment area with antiseptic
- dry surgical sites (e.g., abdomen or arm): use repeated back-and-forth strokes for 30 seconds
- moist surgical sites (e.g., inguinal fold): use repeated back-and-forth strokes for 2 minutes
- allow the solution to completely dry (minimum of 3 minutes on hairless skin; up to 1 hour in hair). Do not blot or wipe away.
- discard prepping materials, including solution soaked materials. It is not necessary to use the entire amount available.

Other information

- store between 15-30°C (59-86°F)
- avoid excessive heat above 40°C (104°F)

Inactive ingredients

Acrylates Copolymer, Acrylates/Octylacrylamide Copolymer, Aminomethyl Propanol, Polyethylene Glycol, USP Purified Water

Questions?

call 1-800-523-0502 (M-F 8 a.m.-5 p.m. CST)

BD PurPrep™ 10.5 mL Applicator Package Label

BD PurPrep™ 10.5 mL Applicator

Povidone-iodine 8.3% w/w (0.83% available iodine) with isopropyl alcohol 72.5% w/w

Patient Preoperative Skin Preparation

Sterile Solution

Applicator is sterile if package is intact

NDC 54365-014-41

Ref 960110

BD PurPrep™ 10.5 mL Applicator Carton Label

BD PurPrep™ 10.5 mL Applicator

Povidone-iodine 8.3% w/w (0.83% available iodine) with isopropyl alcohol 72.5% w/w

Patient Preoperative Skin Preparation

Sterile Solution

Applicator is sterile if package is intact

NDC 54365-014-41

Ref 960110

BD PurPrep™ 26 mL Applicator Package Label

BD PurPrep™ 26 mL Applicator

Povidone-iodine 8.3% w/w (0.83% available iodine) with isopropyl alcohol 72.5% w/w

Patient Preoperative Skin Preparation

Sterile Solution

Applicator is sterile if package is intact

NDC 54365-014-42

Ref 960120